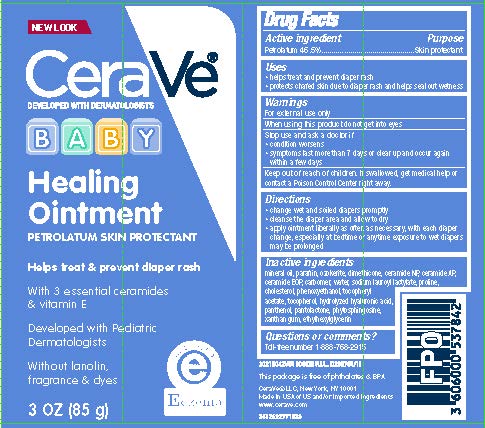 DRUG LABEL: CeraVe Developed with Dermatologists Baby Healing
NDC: 49967-870 | Form: OINTMENT
Manufacturer: L'Oreal USA Products Inc.
Category: otc | Type: HUMAN OTC DRUG LABEL
Date: 20231231

ACTIVE INGREDIENTS: PETROLATUM 46.5 g/100 g
INACTIVE INGREDIENTS: MINERAL OIL; PARAFFIN; CERESIN; DIMETHICONE; HYALURONIC ACID; CERAMIDE 1; CERAMIDE NP; CERAMIDE AP; PHENOXYETHANOL; .ALPHA.-TOCOPHEROL ACETATE; TOCOPHEROL; PHYTOSPHINGOSINE; CHOLESTEROL; SODIUM LAUROYL LACTYLATE; CARBOMER HOMOPOLYMER TYPE A (ALLYL PENTAERYTHRITOL CROSSLINKED); PANTHENOL; PANTOLACTONE; WATER; LAUROYL PROLINE; XANTHAN GUM; ETHYLHEXYLGLYCERIN

Drug Facts

Active ingredients

Petrolatum 46.5%

Purpose

Skin protectant

Uses

■ helps treat and prevent diaper rash

■ protects chafed skin due to diaper rash and helps seal out wetness

Warnings

For external use only

When using this product

do not get into eyes

Stop use and ask a doctor if

- condition worsens
- symptoms last more than 7 days or clear up and occur again within a few days

Keep out of reach of children.

If swallowed, get medical help or contact a Poison Control Center immediately

Directions

- change wet and soiled diapers promptly
- cleanse the diaper area and allow to dry
- apply ointment liberally as often as necessary, with each diaper change, especially at bedtime or anytime exposure to wet diapers may be prolonged

Inactive ingredients

mineral oil, paraffin, ozokerite, dimethicone, ceramide NP, ceramide AP, ceramide EOP, carbomer, water, sodium lauroyl lactylate, proline, cholesterol, phenoxyethanol, tocopheryl acetate, tocopherol, hydrolyzed hyaluronic acid, panthenol, pantolactone, phytosphingosine, xanthan gum, ethylhexylglycerin

Questions?

Toll-free number 1-888-768-2915

www.cerave.com